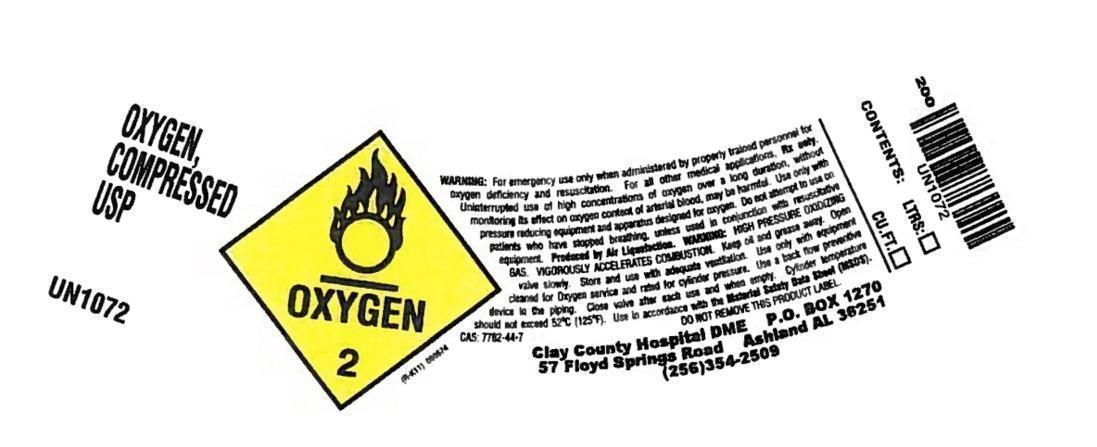 DRUG LABEL: Oxygen
NDC: 66228-002 | Form: GAS
Manufacturer: CLAY COUNTY HOSPITAL DME
Category: prescription | Type: HUMAN PRESCRIPTION DRUG LABEL
Date: 20241021

ACTIVE INGREDIENTS: OXYGEN 990 mL/1 L

Oxygen

PACKAGE LABEL

OXYGEN, COMPRESSED USP

UN1072

OXYGEN 2

WARNING: For emergency use only when administered by properly trained personnel for oxygen deficiency and resuscitation. For all other medical applications, Rx only. Uninterrupted use of high concentrations of oxygen over a long duraction, without monitoring its effect on oxygen content of arterial blood, may be harmful. Use only with pressure reducing equipment and apparatus designed for oxygen. Do not attempt to use on patients who have stopped breathing, unless used in conjunction with resusctitative equipment. Produced by Air Liquefaction. WARNING: HIGH PRESSURE OXIDIZING GAS. VIGOROUSLY ACCELERATES COMBUSTION. Keep oil and grease away. Open valve slowly. Store and use with adequate ventilation. Use only with equipment cleaned for Oxygen service and rated for cylinder pressure. Use a back flow preventive device in the piping. Close valve after each use and when empty. Cylinder temperature should not exceed 52 degrees C (125 degrees F). Use in accordance with the Material Safety Data Sheet (MSDS). CAS: 7782-44-7 DO NOT REMOVE THIS PRODUCT LABEL.

Contents: Ltrs: Cu ft:

Clay County Hospital DMW

PO BOX 1270

57 Floyd Springs Road

Ashland AL 36251

(256) 354-2509